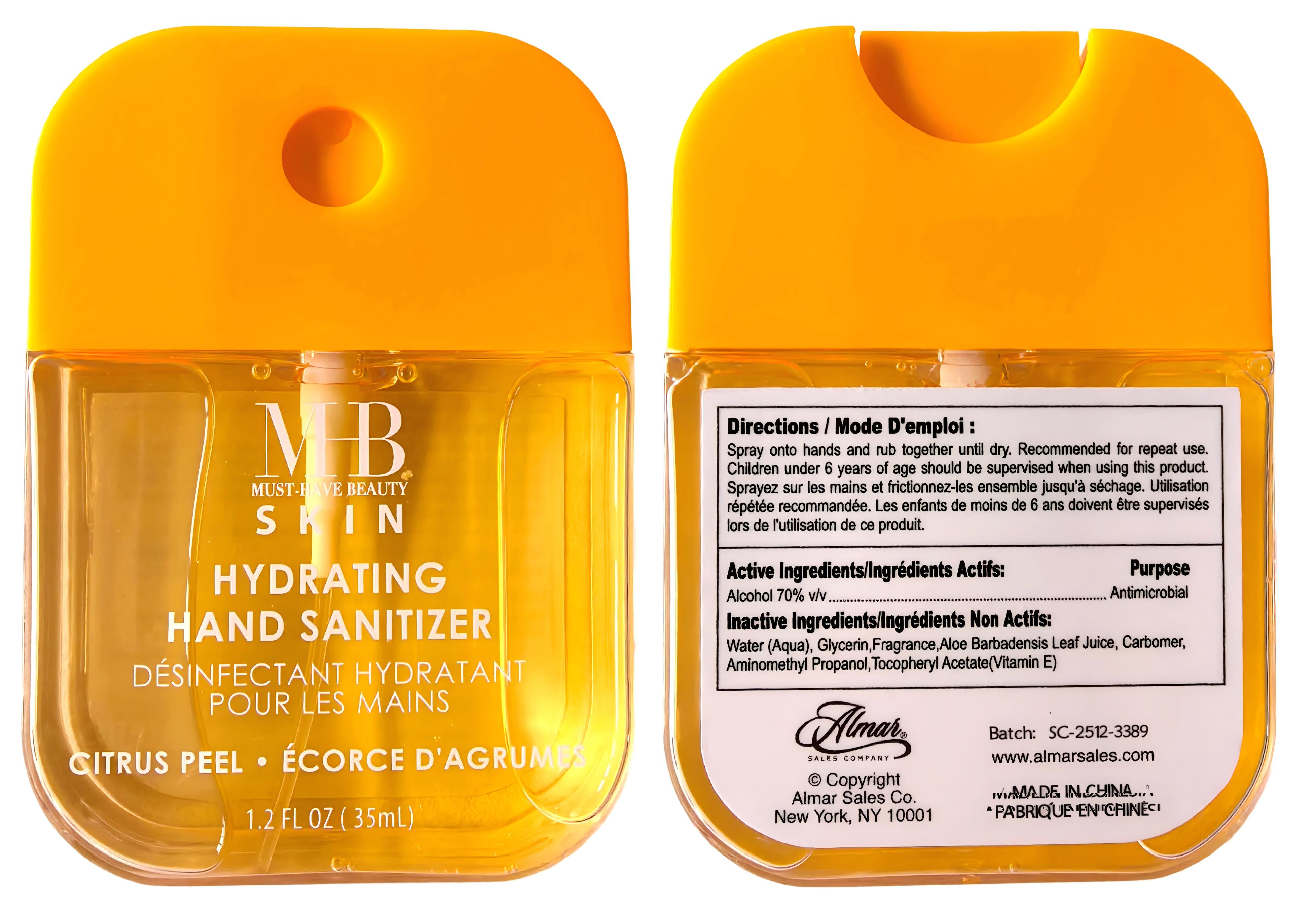 DRUG LABEL: MHB SKIN HYDRATING HAND SANITIZER, CITRUS PEEL
NDC: 75328-212 | Form: SPRAY
Manufacturer: CROWN (YANGZHOU) HEALTH & BEAUTY CO., LTD.
Category: otc | Type: HUMAN OTC DRUG LABEL
Date: 20260125

ACTIVE INGREDIENTS: ALCOHOL 70 mL/100 mL
INACTIVE INGREDIENTS: CI 19140; CARBOMER; AQUA; CI 15985; FRAGRANCE 13576; AMINOMETHYL PROPANOL; ALOE VERA LEAF JUICE; ALPHA-TOCOPHEROL ACETATE; GLYCERIN

Directions:

Spray onto hands and rub together untl dry. Recommended for repeat use.Children under 6 years of age should be supervised when using this product.

Inactive Ingredients:

Water (Aqua),Glycerin,Fragrance,Tocopheryl Acetate (Vitamin E),Carbomer,Aloe Barbadensis Leaf Juice,Aminomethyl Propanol,CI15985, CI19140

Warnings

For external use only, Flammable, keep away from fire or flame.

When using this product:

In case of contact with eyes, rinse eyes thoroughly with water. Avoid contact with broken skin.

Stop use and ask a doctor if:

Irritation and redness occurs.

Keep out of reach of children:

If swallowed, get medical help or contact a Poison Control Center

Active Ingredients:

Ethyl Alcohol 70% v/v Purpose: Antimicrobial.

Use:

Hand sanitizer helps reduce bacteria and the spread of germs.